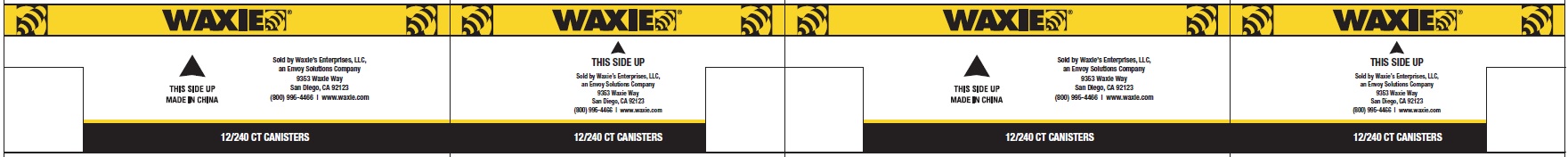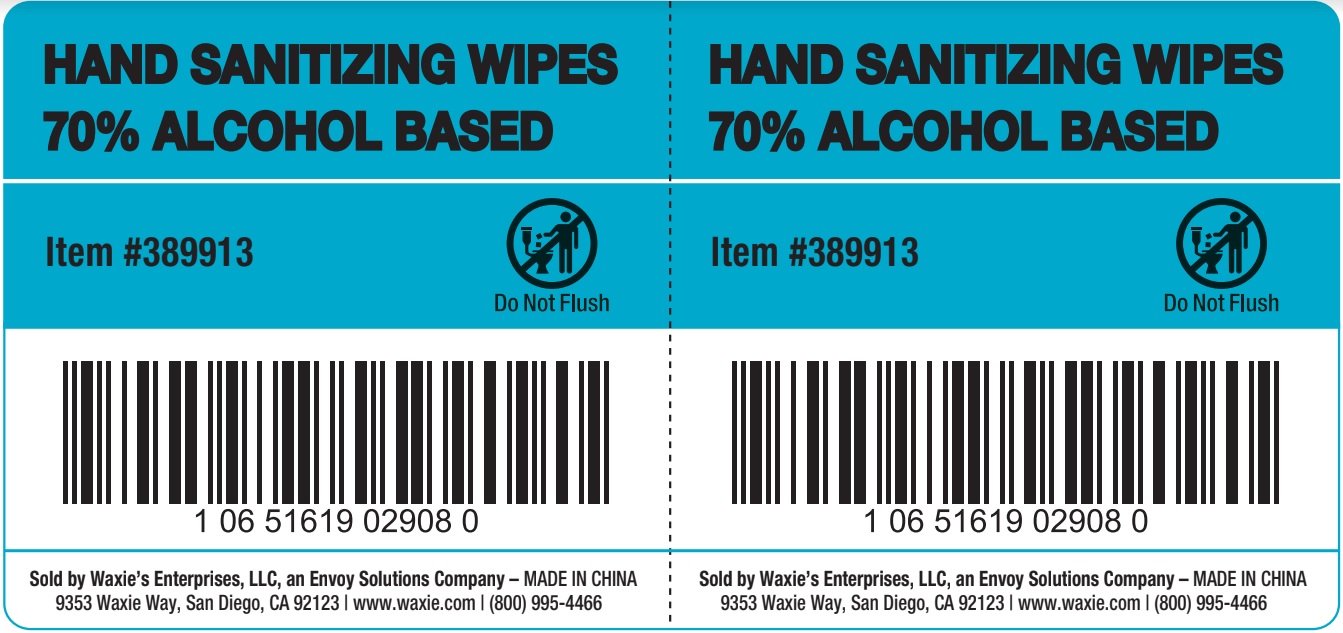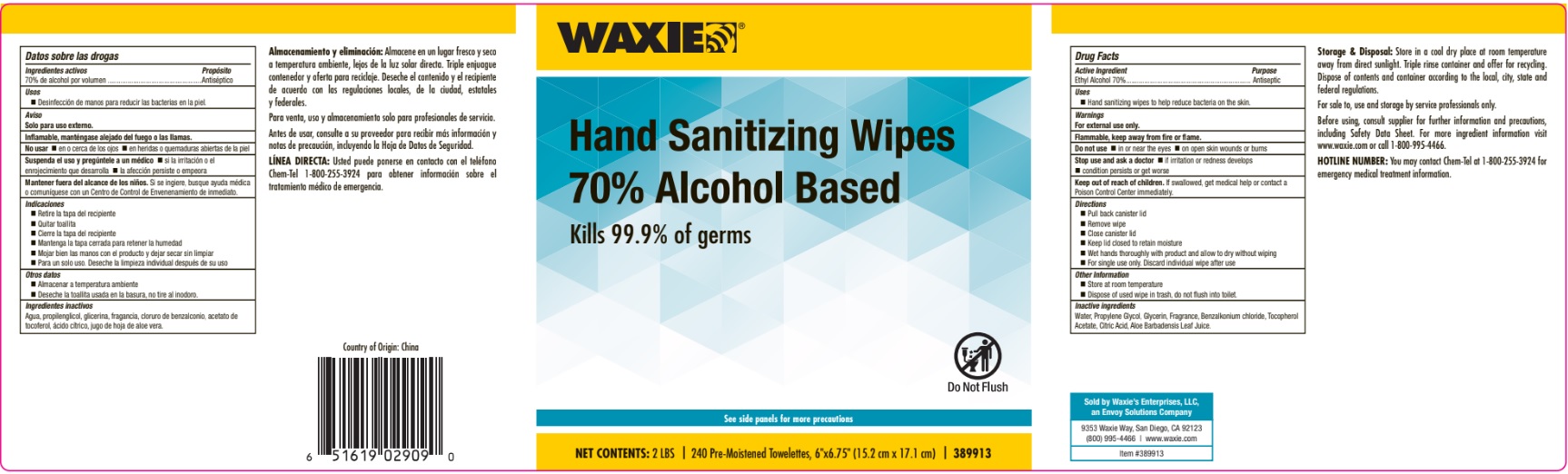 DRUG LABEL: Ethyl Alcohol
NDC: 67151-738 | Form: CLOTH
Manufacturer: Progressive Products, LLC
Category: otc | Type: HUMAN OTC DRUG LABEL
Date: 20230313

ACTIVE INGREDIENTS: ALCOHOL 70 mL/100 mL
INACTIVE INGREDIENTS: ALOE VERA LEAF; CITRIC ACID MONOHYDRATE; PROPYLENE GLYCOL; GLYCERIN; WATER; .ALPHA.-TOCOPHEROL ACETATE

Hand Sanitizing Wipes 240ct

Active Ingredient

Ethyl Alcohol 70%

Purpose

Antiseptic

Uses

- Hand sanitizing wipes to help reduce bacteria on the skin.

Warnings

For External use only.

Flammable

Keep away from fire or flame.

Do not use

- in or near the eyes
- on open skin wounds or burns

Stop use and ask a doctor

- if irritation or redness develops
- condition persists or get worse

Keep out of reach of children

If swallowed, get medical help or contact a Poison Control Center immediately.

Directions

- Pull back canster lid
- Remove wipe
- Close canister lid
- Keep lid closed to retain moisture
- Wet hands thoroughly with product and allow to dry without wiping
- For single use only. Discard individual wipe after use

Other information

- Store at room temperature
- Dispose of used wipe in trash, do not flush into toilet.

Inactive ingredients

Water, Propylene Glycol, Glycerin, Fragrance, Benzalkonium chloride, Tocopherol Acetate, Citric Acid, Aloe Barbadensis Leaf Juice

Principal Display Panel

WAXIE

Hand Sanitizing Wipes

70% Alcohol Based

Kills 99.9% of germs

12/240 CT CANISTERS